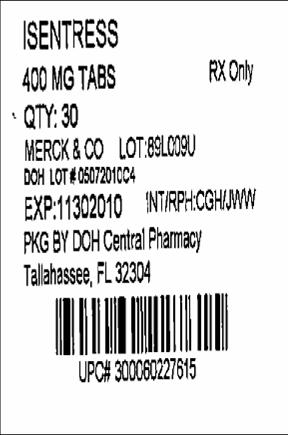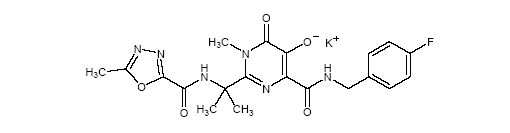 DRUG LABEL: ISENTRESS
NDC: 53808-0650 | Form: TABLET, FILM COATED
Manufacturer: State of Florida DOH Central Pharmacy
Category: prescription | Type: HUMAN PRESCRIPTION DRUG LABEL
Date: 20100811

ACTIVE INGREDIENTS: RALTEGRAVIR POTASSIUM 400 mg/1 1
INACTIVE INGREDIENTS: FERROSOFERRIC OXIDE; BUTYLATED HYDROXYTOLUENE; ANHYDROUS DIBASIC CALCIUM PHOSPHATE; HYPROMELLOSE; LACTOSE MONOHYDRATE; MAGNESIUM STEARATE; CELLULOSE, MICROCRYSTALLINE; POLOXAMER 407; POLYETHYLENE GLYCOL 3350; POLYVINYL ALCOHOL; FERRIC OXIDE RED; SODIUM STEARYL FUMARATE; TALC; TITANIUM DIOXIDE

HIGHLIGHTS OF PRESCRIBING INFORMATION

These highlights do not include all the information needed to use ISENTRESS safely and effectively. See full prescribing information for ISENTRESS.
ISENTRESS (raltegravir) Tablets
Initial U.S. Approval: 2007

RECENT MAJOR CHANGES

Indications And Usage (1) 07/2009

Dosage And Administration (2) 01/2009

Warnings And Precautions (5.2) - removal 07/2009

1 INDICATIONS AND USAGE

ISENTRESS® is a human immunodeficiency virus integrase strand transfer inhibitor (HIV-1 INSTI) indicated:

- In combination with other antiretroviral agents for the treatment of HIV-1 infection in adult patients (1).

The safety and efficacy of ISENTRESS have not been established in pediatric patients (1).

2 DOSAGE AND ADMINISTRATION

- 400 mg administered orally, twice daily with or without food (2).
- During coadministration with rifampin, 800 mg twice daily (2).

3 DOSAGE FORMS AND STRENGTHS

Tablets: 400 mg (3).

4 CONTRAINDICATIONS

None (4)

5 WARNINGS AND PRECAUTIONS

Monitor for Immune Reconstitution Syndrome (5.1).

6 ADVERSE REACTIONS

- The most common adverse reactions of moderate to severe intensity (≥2%) which occurred at a higher rate than the comparator are insomnia, headache, nausea, asthenia and fatigue (6.1).
- Creatine kinase elevations were observed in subjects who received ISENTRESS. Myopathy and rhabdomyolysis have been reported; however, the relationship of ISENTRESS to these events is not known. Use with caution in patients at increased risk of myopathy or rhabdomyolysis, such as patients receiving concomitant medications known to cause these conditions (6.1).
  To report SUSPECTED ADVERSE REACTIONS, contact Merck & Co., Inc. at 1-877-888-4231 or FDA at 1-800-FDA-1088 or www.fda.gov/medwatch.

7 DRUG INTERACTIONS

- Coadministration of ISENTRESS with drugs that are strong inducers of UGT1A1 may result in reduced plasma concentrations of raltegravir (7.2).

8 USE IN SPECIFIC POPULATIONS

Pregnancy:

- ISENTRESS should be used during pregnancy only if the potential benefit justifies the potential risk to the fetus. Physicians are encouraged to register pregnant women exposed to ISENTRESS by calling 1-800-258-4263 so that Merck can monitor maternal and fetal outcomes (8.1).

Nursing Mothers:

- Breast-feeding is not recommended while taking ISENTRESS (8.3).

FULL PRESCRIBING INFORMATION

1 INDICATIONS AND USAGE

ISENTRESS [Registered trademark of MERCK & CO., Inc. COPYRIGHT © 2007, 2009 MERCK & CO., Inc. All rights reserved] is indicated in combination with other anti-retroviral agents for the treatment of human immunodeficiency virus (HIV-1) infection in adult patients.

This indication is based on analyses of plasma HIV-1 RNA levels up through 48 weeks in three double-blind controlled studies of ISENTRESS. Two of these studies were conducted in clinically advanced, 3-class antiretroviral (NNRTI, NRTI, PI) treatment-experienced adults and one was conducted in treatment-naïve adults.

The use of other active agents with ISENTRESS is associated with a greater likelihood of treatment response [see Clinical Studies (14)].

The safety and efficacy of ISENTRESS have not been established in pediatric patients.

2 DOSAGE AND ADMINISTRATION

For the treatment of patients with HIV-1 infection, the dosage of ISENTRESS is 400 mg administered orally, twice daily with or without food. During coadministration with rifampin, the recommended dosage of ISENTRESS is 800 mg twice daily with or without food.

3 DOSAGE FORMS AND STRENGTHS

400 mg pink, oval shaped, film-coated tablets with "227" on one side.

4 CONTRAINDICATIONS

None

5 WARNINGS AND PRECAUTIONS

5.1 Immune Reconstitution Syndrome

During the initial phase of treatment, patients responding to antiretroviral therapy may develop an inflammatory response to indolent or residual opportunistic infections (such as Mycobacterium avium complex, cytomegalovirus, Pneumocystis jiroveci pneumonia, Mycobacterium tuberculosis, or reactivation of varicella zoster virus), which may necessitate further evaluation and treatment.

6 ADVERSE REACTIONS

6.1 Clinical Trials Experience

Because clinical trials are conducted under widely varying conditions, adverse reaction rates observed in the clinical trials of a drug cannot be directly compared to rates in the clinical trials of another drug and may not reflect the rates observed in practice.

Treatment-Naïve Studies

The following safety assessment of ISENTRESS in treatment-naïve subjects is based on the randomized double-blind active controlled study of treatment-naïve subjects, STARTMRK (Protocol 021) with ISENTRESS 400 mg twice daily in combination with a fixed dose of emtricitabine 200 mg (+) tenofovir 300 mg, (N=281) versus efavirenz (EFV) 600 mg at bedtime in combination with emtricitabine (+) tenofovir, (N=282). During double-blind treatment, the total follow-up for subjects receiving ISENTRESS 400 mg twice daily + emtricitabine (+) tenofovir was 247 patient-years and 241 patient-years for subjects receiving efavirenz 600 mg at bedtime + emtricitabine (+) tenofovir.

In Protocol 021, the rate of discontinuation of therapy due to adverse reactions was 3% in subjects receiving ISENTRESS + emtricitabine (+) tenofovir and 6% in subjects receiving efavirenz + emtricitabine (+) tenofovir.

The clinical adverse drug reactions (ADRs) listed below were considered by investigators to be causally related to ISENTRESS + emtricitabine (+) tenofovir or efavirenz + emtricitabine (+) tenofovir. Clinical ADRs of moderate to severe intensity occurring in ≥2% of treatment-naïve subjects treated with ISENTRESS and occurring at a higher rate than efavirenz are presented in Table 1.

Table 1: Adverse Reactions [Includes adverse experiences considered by investigators to be at least possibly, probably, or definitely related to the drug] of Moderate to Severe Intensity [Intensities are defined as follows: Moderate (discomfort enough to cause interference with usual activity); Severe (incapacitating with inability to work or do usual activity).] Occurring in ≥2% of Treatment-Naïve Adult Subjects Receiving ISENTRESS and at a Higher Rate Compared to Efavirenz (48 Week Analysis)
System Organ Class, Preferred Term | Randomized Study Protocol 021
System Organ Class, Preferred Term | ISENTRESS 400 mg Twice Daily + Emtricitabine (+) Tenofovir (n = 281) [n = total number of subjects per treatment group] % | Efavirenz 600 mg At Bedtime + Emtricitabine (+) Tenofovir (n = 282) %
Psychiatric Disorders
Insomnia | 4 | 3

Less Common Adverse Reactions

The following ADRs occurred in <2% of subjects receiving ISENTRESS + emtricitabine (+) tenofovir. These events have been included because of their seriousness, increased frequency on ISENTRESS compared with efavirenz or investigator's assessment of potential causal relationship.

General Disorders and Administration Site Conditions: fatigue

Psychiatric Disorders: abnormal dreams

Laboratory Abnormalities

The percentages of adult subjects treated with ISENTRESS 400 mg twice daily or efavirenz in Protocol 021 with selected Grades 2 to 4 laboratory abnormalities that represent a worsening from baseline are presented in Table 2.

Table 2: Selected Grade 2 to 4 Laboratory Abnormalities Reported in Treatment-Naïve Subjects (48 Week Analysis)
 |  | Randomized Study Protocol 021
Laboratory Parameter Preferred Term (Unit) | Limit | ISENTRESS 400 mg Twice Daily + Emtricitabine (+) Tenofovir (N = 281) | Efavirenz 600 mg At Bedtime + Emtricitabine (+) Tenofovir (N = 282)
Hematology
Absolute neutrophil count (10^3/μL)
Grade 2 | 0.75 - 0.999 | 3% | 3%
Grade 3 | 0.50 - 0.749 | 1% | <1%
Grade 4 | <0.50 | <1% | 0%
Hemoglobin (gm/dL)
Grade 2 | 7.5 - 8.4 | <1% | <1%
Grade 3 | 6.5 - 7.4 | <1% | <1%
Grade 4 | <6.5 | 0% | 0%
Platelet count (10^3/μL)
Grade 2 | 50 - 99.999 | 2% | 0%
Grade 3 | 25 - 49.999 | 0% | <1%
Grade 4 | <25 | 0% | .0%
Blood chemistry
Fasting (non-random) serum glucose test (mg/dL)
Grade 2 | 126 - 250 | 2% | 3%
Grade 3 | 251 - 500 | <1% | 0%
Grade 4 | >500 | 0% | 0%
Total serum bilirubin
Grade 2 | 1.6 - 2.5 x ULN | 4% | 0%
Grade 3 | 2.6 - 5.0 x ULN | <1% | 0%
Grade 4 | >5.0 x ULN | 0% | 0%
Serum aspartate aminotransferase
Grade 2 | 2.6 - 5.0 x ULN | 3% | 4%
Grade 3 | 5.1 - 10.0 x ULN | 1% | 1%
Grade 4 | >10.0 x ULN | <1% | <1%
Serum alanine aminotransferase
Grade 2 | 2.6 - 5.0 x ULN | 4% | 6%
Grade 3 | 5.1 - 10.0 x ULN | <1% | 2%
Grade 4 | >10.0 x ULN | <1% | <1%
Serum alkaline phosphatase
Grade 2 | 2.6 - 5.0 x ULN | <1% | 2%
Grade 3 | 5.1 - 10.0 x ULN | 0% | <1%
Grade 4 | >10.0 x ULN | 0% | 0%
ULN = Upper limit of normal range

Lipids, Change from Baseline

Changes from baseline in fasting lipids are shown in Table 3.

Table 3: Lipid Values, Mean Change from Baseline, Protocol 021
Laboratory Parameter Preferred Term | ISENTRESS 400 mg; Twice Daily + Emtricitabine (+) Tenofovir; N = 281 |  |  | Efavirenz 600 mg; At Bedtime + Emtricitabine (+) Tenofovir; N = 282
 |  |  | Change from Baseline at Week 48 |  |  | Change from Baseline at Week 48
 | Baseline Mean(mg/dL) | Week 48 Mean(mg/dL) | Mean Change (mg/dL) | Baseline Mean(mg/dL) | Week 48 Mean(mg/dL) | Mean Change (mg/dL)
LDL-Cholesterol [Fasting (non-random) laboratory tests.] | 97 | 103 | 6 | 92 | 108 | 16
HDL-Cholesterol | 38 | 42 | 4 | 38 | 48 | 10
Total Cholesterol | 159 | 169 | 10 | 156 | 188 | 33
Triglyceride | 125 | 122 | -3 | 136 | 174 | 37
Notes:
N = Number of subjects in the treatment group. The analysis is based on all available data.
If subjects initiated or increased serum lipid-reducing agents, the last available lipid values prior to the change in therapy were used in the analysis. If the missing data was due to other reasons, subjects were censored thereafter for the analysis.
At baseline, serum lipid-reducing agents were used in 5% of subjects in the group receiving ISENTRESS and 3% in the efavirenz group. Through Week 48, serum lipid-reducing agents were used in 6% of subjects in the group receiving ISENTRESS and 6% in the efavirenz group.

Treatment-Experienced Studies

The safety assessment of ISENTRESS in treatment-experienced subjects is based on the pooled safety data from the randomized, double-blind, placebo-controlled trials, BENCHMRK 1 and BENCHMRK 2 (Protocols 018 and 019) in antiretroviral treatment-experienced HIV-1 infected adult subjects. A total of 462 subjects received the recommended dose of ISENTRESS 400 mg twice daily in combination with optimized background therapy (OBT) compared to 237 subjects taking placebo in combination with OBT. The median duration of therapy in these trials was 48 weeks for subjects receiving ISENTRESS and 38 weeks for subjects receiving placebo. The total exposure to ISENTRESS was 387 patient-years versus 156 patient-years on placebo. The rates of discontinuation due to adverse events were 2% in subjects receiving ISENTRESS and 3% in subjects receiving placebo.

Clinical ADRs were considered by investigators to be causally related to ISENTRESS + OBT or placebo + OBT. Clinical ADRs of moderate to severe intensity occurring in ≥2% of subjects treated with ISENTRESS and occurring at a higher exposure adjusted rate compared to placebo are presented in Table 4.

Table 4: Adverse Drug Reactions [Includes adverse reactions at least possibly, probably, or definitely related to the drug.] of Moderate to Severe Intensity [Intensities are defined as follows: Moderate (discomfort enough to cause interference with usual activity); Severe (incapacitating with inability to work or do usual activity).] Occurring in ≥2% of Treatment-Experienced Adult Subjects Receiving ISENTRESS and at a Higher Exposure Adjusted Rate Compared to Placebo (48 Week Analysis, Exposure Adjusted Incidence Rates)
System Organ Class, Adverse Reactions | Randomized Studies Protocol 018 and 019
System Organ Class, Adverse Reactions | ISENTRESS 400 mg Twice Daily + OBT (n = 462) [n=total number of subjects per treatment group.] | Placebo + OBT (n = 237)
 | Rate per 100 Patient-Years | Rate per 100 Patient-Years
Nervous System Disorders
Headache | 3 | 1
Gastrointestinal Disorders
Nausea | 2 | 1
General Disorders and Administration Site Conditions
Asthenia | 2 | 1
Fatigue | 2 | 1

Less Common Adverse Reactions

The following ADRs occurred in <2% of subjects receiving ISENTRESS + OBT. These events have been included because of either their seriousness, increased frequency on ISENTRESS compared with placebo or investigator's assessment of potential causal relationship.

Gastrointestinal Disorders: abdominal pain, gastritis

Hepatobiliary Disorders: hepatitis

Immune System Disorders: hypersensitivity

Infections and Infestations: genital herpes, herpes zoster

Nervous System Disorders: dizziness

Renal and Urinary Disorders: renal failure

Laboratory Abnormalities

The percentages of adult subjects treated with ISENTRESS 400 mg twice daily or placebo in Protocols 018 and 019 with selected Grade 2 to 4 laboratory abnormalities representing a worsening from baseline are presented in Table 5.

Table 5: Selected Grade 2 to 4 Laboratory Abnormalities Reported in Treatment-Experienced Subjects (48 Week Analysis)
 |  | Randomized Studies Protocol 018 and 019
Laboratory Parameter Preferred Term (Unit) | Limit | ISENTRESS 400 mg Twice Daily + OBT (N = 462) | Placebo + OBT (N = 237)
Hematology
Absolute neutrophil count (10^3/μL)
Grade 2 | 0.75 - 0.999 | 3% | 5%
Grade 3 | 0.50 - 0.749 | 3% | 3%
Grade 4 | <0.50 | 1% | <1%
Hemoglobin (gm/dL)
Grade 2 | 7.5 - 8.4 | 1% | 3%
Grade 3 | 6.5 - 7.4 | 1% | <1%
Grade 4 | <6.5 | <1% | 0%
Platelet count (10^3/μL)
Grade 2 | 50 - 99.999 | 3% | 5%
Grade 3 | 25 - 49.999 | 1% | <1%
Grade 4 | <25 | 1% | <1%
Blood chemistry
Fasting (non-random) serum glucose test (mg/dL)
Grade 2 | 126 – 250 | 8% | 5%
Grade 3 | 251 – 500 | 2% | 1%
Grade 4 | >500 | 0% | 0%
Total serum bilirubin
Grade 2 | 1.6 - 2.5 x ULN | 5% | 3%
Grade 3 | 2.6 - 5.0 x ULN | 2% | 2%
Grade 4 | >5.0 x ULN | 1% | 0%
Serum aspartate aminotransferase
Grade 2 | 2.6 - 5.0 x ULN | 8% | 6%
Grade 3 | 5.1 - 10.0 x ULN | 3% | 3%
Grade 4 | >10.0 x ULN | <1% | 1%
Serum alanine aminotransferase
Grade 2 | 2.6 - 5.0 x ULN | 7% | 8%
Grade 3 | 5.1 - 10.0 x ULN | 3% | 2%
Grade 4 | >10.0 x ULN | 1% | 2%
Serum alkaline phosphatase
Grade 2 | 2.6 - 5.0 x ULN | 2% | <1%
Grade 3 | 5.1 - 10.0 x ULN | <1% | 1%
Grade 4 | >10.0 x ULN | 1% | <1%
Serum pancreatic amylase test
Grade 2 | 1.6 - 2.0 x ULN | 2% | 1%
Grade 3 | 2.1 - 5.0 x ULN | 3% | 3%
Grade 4 | >5.0 x ULN | <1% | 0%
Serum lipase test
Grade 2 | 1.6 - 3.0 x ULN | 4% | 3%
Grade 3 | 3.1 - 5.0 x ULN | 1% | <1%
Grade 4 | >5.0 x ULN | 0% | 0%
Serum creatine kinase
Grade 2 | 6.0 - 9.9 x ULN | 2% | 2%
Grade 3 | 10.0 - 19.9 x ULN | 3% | 3%
Grade 4 | ≥20.0 x ULN | 2% | 1%
ULN = Upper limit of normal range

Selected Adverse Events

Regardless of Drug Relationship

Cancers were reported in treatment-experienced subjects who initiated ISENTRESS or placebo, both with OBT, and in treatment-naïve subjects who initiated ISENTRESS or efavirenz, both with emtricitabine (+) tenofovir; several were recurrent. The types and rates of specific cancers were those expected in a highly immunodeficient population (many had CD4+ counts below 50 cells/mm^3 and most had prior AIDS diagnoses). The risk of developing cancer in these studies was similar in the group receiving ISENTRESS and the group receiving the comparator.

Grade 2-4 creatine kinase laboratory abnormalities were observed in subjects treated with ISENTRESS (see Table 5). Myopathy and rhabdomyolysis have been reported; however, the relationship of ISENTRESS to these events is not known. Use with caution in patients at increased risk of myopathy or rhabdomyolysis, such as patients receiving concomitant medications known to cause these conditions.

Patients with Co-existing Conditions

Patients Co-infected with Hepatitis B and/or Hepatitis C Virus

In the randomized, double-blind, placebo-controlled trials, treatment-experienced subjects (N = 114/699 or 16%) and treatment-naïve subjects (N = 34/563 or 6%) with chronic (but not acute) active hepatitis B and/or hepatitis C virus co-infection were permitted to enroll provided that baseline liver function tests did not exceed 5 times the upper limit of normal (ULN). In general the safety profile of ISENTRESS in subjects with hepatitis B and/or hepatitis C virus co-infection was similar to that in subjects without hepatitis B and/or hepatitis C virus co-infection, although the rates of AST and ALT abnormalities were higher in the subgroup with hepatitis B and/or hepatitis C virus co-infection for all treatment groups. In treatment-experienced subjects, Grade 2 or higher laboratory abnormalities that represent a worsening Grade from baseline of AST, ALT or total bilirubin occurred in 25%, 31% and 12%, respectively, of co-infected subjects treated with ISENTRESS as compared to 8%, 7% and 8% of all other subjects treated with ISENTRESS. In treatment-naïve subjects, Grade 2 or higher laboratory abnormalities that represent a worsening Grade from baseline of AST, ALT or total bilirubin occurred in 17%, 22% and 11%, respectively, of co-infected subjects treated with ISENTRESS as compared to 4%, 4% and 3% of all other subjects treated with ISENTRESS.

6.2 Postmarketing Experience

The following adverse reactions have been identified during postapproval use of ISENTRESS. Because these reactions are reported voluntarily from a population of uncertain size, it is not always possible to reliably estimate their frequency or establish a causal relationship to drug exposure.

Psychiatric Disorders: anxiety, depression (particularly in patients with a pre-existing history of psychiatric illness), including suicidal ideation and behaviors, paranoia

Skin and Subcutaneous Tissue Disorders: rash, Stevens-Johnson syndrome

7 DRUG INTERACTIONS

7.1 Effect of Raltegravir on the Pharmacokinetics of Other Agents

Raltegravir does not inhibit (IC50>100 µM) CYP1A2, CYP2B6, CYP2C8, CYP2C9, CYP2C19, CYP2D6 or CYP3A in vitro. Moreover, in vitro, raltegravir did not induce CYP1A2, CYP2B6 or CYP3A4. A midazolam drug interaction study confirmed the low propensity of raltegravir to alter the pharmacokinetics of agents metabolized by CYP3A4 in vivo by demonstrating a lack of effect of raltegravir on the pharmacokinetics of midazolam, a sensitive CYP3A4 substrate. Similarly, raltegravir is not an inhibitor (IC50>50 µM) of the UDP-glucuronosyltransferases (UGT) tested (UGT1A1, UGT2B7), and raltegravir does not inhibit P-glycoprotein-mediated transport. Based on these data, ISENTRESS is not expected to affect the pharmacokinetics of drugs that are substrates of these enzymes or P-glycoprotein (e.g., protease inhibitors, NNRTIs, opioid analgesics, statins, azole antifungals, proton pump inhibitors and anti-erectile dysfunction agents).

In drug interaction studies, raltegravir did not have a clinically meaningful effect on the pharmacokinetics of the following: hormonal contraceptives, methadone, lamivudine, tenofovir, etravirine.

7.2 Effect of Other Agents on the Pharmacokinetics of Raltegravir

Raltegravir is not a substrate of cytochrome P450 (CYP) enzymes. Based on in vivo and in vitro studies, raltegravir is eliminated mainly by metabolism via a UGT1A1-mediated glucuronidation pathway.

Rifampin, a strong inducer of UGT1A1, reduces plasma concentrations of ISENTRESS. Therefore, the dose of ISENTRESS should be increased during coadministration with rifampin [see Dosage and Administration (2)]. The impact of other inducers of drug metabolizing enzymes, such as phenytoin and phenobarbital, on UGT1A1 is unknown.

Coadministration of ISENTRESS with drugs that inhibit UGT1A1 may increase plasma levels of raltegravir.

Selected drug interactions are presented in Table 6 [see Clinical Pharmacology (12.3)].

Table 6: Selected Drug Interactions
Concomitant Drug Class:; Drug Name | Effect on; Concentration; of Raltegravir | Clinical Comment
HIV-1-Antiviral Agents
atazanavir | ↑ | Atazanavir, a strong inhibitor of UGT1A1, increases plasma concentrations of raltegravir. However, since concomitant use of ISENTRESS with atazanavir/ritonavir did not result in a unique safety signal in Phase 3 studies, no dose adjustment is recommended.
atazanavir/ritonavir | ↑ | Atazanavir/ritonavir increases plasma concentrations of raltegravir. However, since concomitant use of ISENTRESS with atazanavir/ritonavir did not result in a unique safety signal in Phase 3 studies, no dose adjustment is recommended.
efavirenz | ↓ | Efavirenz reduces plasma concentrations of raltegravir. The clinical significance of this interaction has not been directly assessed.
etravirine | ↓ | Etravirine reduces plasma concentrations of raltegravir. The clinical significance of this interaction has not been directly assessed.
tipranavir/ritonavir | ↓ | Tipranavir/ritonavir reduces plasma concentrations of raltegravir. However, since comparable efficacy was observed for this combination relative to other ISENTRESS-containing regimens in Phase 3 studies 018 and 019, no dose adjustment is recommended.
Other Agents
omeprazole | ↑ | Coadministration of medicinal products that increase gastric pH (e.g., omeprazole) may increase raltegravir levels based on increased raltegravir solubility at higher pH. However, since concomitant use of ISENTRESS with proton pump inhibitors and H2 blockers did not result in a unique safety signal in Phase 3 studies, no dose adjustment is recommended.
rifampin | ↓ | Rifampin, a strong inducer of UGT1A1, reduces plasma concentrations of raltegravir. The recommended dosage of ISENTRESS is 800 mg twice daily during coadministration with rifampin.

8 USE IN SPECIFIC POPULATIONS

8.1 Pregnancy

Pregnancy Category C

ISENTRESS should be used during pregnancy only if the potential benefit justifies the potential risk to the fetus. There are no adequate and well-controlled studies in pregnant women. In addition, there have been no pharmacokinetic studies conducted in pregnant patients.

Developmental toxicity studies were performed in rabbits (at oral doses up to 1000 mg/kg/day) and rats (at oral doses up to 600 mg/kg/day). The reproductive toxicity study in rats was performed with pre-, peri-, and postnatal evaluation. The highest doses in these studies produced systemic exposures in these species approximately 3- to 4-fold the exposure at the recommended human dose. In both rabbits and rats, no treatment-related effects on embryonic/fetal survival or fetal weights were observed. In addition, no treatment-related external, visceral, or skeletal changes were observed in rabbits. However, treatment-related increases over controls in the incidence of supernumerary ribs were seen in rats at 600 mg/kg/day (exposures 3-fold the exposure at the recommended human dose).

Placenta transfer of drug was demonstrated in both rats and rabbits. At a maternal dose of 600 mg/kg/day in rats, mean drug concentrations in fetal plasma were approximately 1.5- to 2.5-fold greater than in maternal plasma at 1 hour and 24 hours postdose, respectively. Mean drug concentrations in fetal plasma were approximately 2% of the mean maternal concentration at both 1 and 24 hours postdose at a maternal dose of 1000 mg/kg/day in rabbits.

Antiretroviral Pregnancy Registry

To monitor maternal-fetal outcomes of pregnant patients exposed to ISENTRESS, an Antiretroviral Pregnancy Registry has been established. Physicians are encouraged to register patients by calling 1-800-258-4263.

8.3 Nursing Mothers

Breast-feeding is not recommended while taking ISENTRESS. In addition, it is recommended that HIV-1-infected mothers not breast-feed their infants to avoid risking postnatal transmission of HIV-1.

It is not known whether raltegravir is secreted in human milk. However, raltegravir is secreted in the milk of lactating rats. Mean drug concentrations in milk were approximately 3-fold greater than those in maternal plasma at a maternal dose of 600 mg/kg/day in rats. There were no effects in rat offspring attributable to exposure of ISENTRESS through the milk.

8.4 Pediatric Use

Safety and effectiveness of ISENTRESS in pediatric patients have not been established.

8.5 Geriatric Use

Clinical studies of ISENTRESS did not include sufficient numbers of subjects aged 65 and over to determine whether they respond differently from younger subjects. Other reported clinical experience has not identified differences in responses between the elderly and younger subjects. In general, dose selection for an elderly patient should be cautious, reflecting the greater frequency of decreased hepatic, renal, or cardiac function, and of concomitant disease or other drug therapy.

8.6 Use in Patients with Hepatic Impairment

No clinically important pharmacokinetic differences between subjects with moderate hepatic impairment and healthy subjects were observed. No dosage adjustment is necessary for patients with mild to moderate hepatic impairment. The effect of severe hepatic impairment on the pharmacokinetics of raltegravir has not been studied [see Clinical Pharmacology (12.3)].

8.7 Use in Patients with Renal Impairment

No clinically important pharmacokinetic differences between subjects with severe renal impairment and healthy subjects were observed. No dosage adjustment is necessary [see Clinical Pharmacology (12.3)].

10 OVERDOSAGE

No specific information is available on the treatment of overdosage with ISENTRESS. Doses as high as 1600-mg single dose and 800-mg twice-daily multiple doses were studied in healthy volunteers without evidence of toxicity. Occasional doses of 1800 mg per day were taken in the clinical studies of HIV-1 infected subjects without evidence of toxicity.

In the event of an overdose, it is reasonable to employ the standard supportive measures, e.g., remove unabsorbed material from the gastrointestinal tract, employ clinical monitoring (including obtaining an electrocardiogram), and institute supportive therapy if required. The extent to which ISENTRESS may be dialyzable is unknown.

11 DESCRIPTION

ISENTRESS contains raltegravir potassium, a human immunodeficiency virus integrase strand transfer inhibitor. The chemical name for raltegravir potassium is N-[(4-Fluorophenyl)methyl]-1,6-dihydro-5-hydroxy-1-methyl-2-[1-methyl-1-[[(5-methyl-1,3,4-oxadiazol-2-yl)carbonyl]amino]ethyl]-6-oxo-4-pyrimidinecarboxamide monopotassium salt.

The empirical formula is C20H20FKN6O5 and the molecular weight is 482.51. The structural formula is:

Raltegravir potassium is a white to off-white powder. It is soluble in water, slightly soluble in methanol, very slightly soluble in ethanol and acetonitrile and insoluble in isopropanol.

Each film-coated tablet of ISENTRESS for oral administration contains 434.4 mg of raltegravir potassium (as salt), equivalent to 400 mg of raltegravir (free phenol) and the following inactive ingredients: microcrystalline cellulose, lactose monohydrate, calcium phosphate dibasic anhydrous, hypromellose 2208, poloxamer 407 (contains 0.01% butylated hydroxytoluene as antioxidant), sodium stearyl fumarate, magnesium stearate. In addition, the film coating contains the following inactive ingredients: polyvinyl alcohol, titanium dioxide, polyethylene glycol 3350, talc, red iron oxide and black iron oxide.

12 CLINICAL PHARMACOLOGY

12.1 Mechanism of Action

Raltegravir is an HIV-1 antiviral drug [see Clinical Pharmacology (12.4)].

12.2 Pharmacodynamics

In a monotherapy study raltegravir (400 mg twice daily) demonstrated rapid antiviral activity with mean viral load reduction of 1.66 log10 copies/mL by Day 10.

In the randomized, double-blind, placebo-controlled, dose-ranged trial, Protocol 005, and Protocols 018 and 019, antiviral responses were similar among subjects regardless of dose.

Effects on Electrocardiogram

In a randomized, placebo-controlled, crossover study, 31 healthy subjects were administered a single oral supratherapeutic dose of raltegravir 1600 mg and placebo. Peak raltegravir plasma concentrations were approximately 4-fold higher than the peak concentrations following a 400 mg dose. ISENTRESS did not appear to prolong the QTc interval for 12 hours postdose. After baseline and placebo adjustment, the maximum mean QTc change was -0.4 msec (1-sided 95% upper Cl: 3.1 msec).

12.3 Pharmacokinetics

Absorption

Raltegravir is absorbed with a Tmax of approximately 3 hours postdose in the fasted state. Raltegravir AUC and Cmax increase dose proportionally over the dose range 100 mg to 1600 mg. Raltegravir C12hr increases dose proportionally over the dose range of 100 to 800 mg and increases slightly less than dose proportionally over the dose range 100 mg to 1600 mg. With twice-daily dosing, pharmacokinetic steady state is achieved within approximately the first 2 days of dosing. There is little to no accumulation in AUC and Cmax. The average accumulation ratio for C12hr ranged from approximately 1.2 to 1.6.

The absolute bioavailability of raltegravir has not been established.

In subjects who received 400 mg twice daily alone, raltegravir drug exposures were characterized by a geometric mean AUC0-12hr of 14.3 μM●hr and C12hr of 142 nM.

Considerable variability was observed in the pharmacokinetics of raltegravir. For observed C12hr in Protocols 018 and 019, the coefficient of variation (CV) for inter-subject variability = 212% and the CV for intra-subject variability = 122%.

Effect of Food on Oral Absorption

ISENTRESS may be administered with or without food. Raltegravir was administered without regard to food in the pivotal safety and efficacy studies in HIV-1-infected patients. The effect of consumption of low-, moderate- and high-fat meals on steady-state raltegravir pharmacokinetics was assessed in healthy volunteers. Administration of multiple doses of raltegravir following a moderate-fat meal (600 Kcal, 21 g fat) did not affect raltegravir AUC to a clinically meaningful degree with an increase of 13% relative to fasting. Raltegravir C12hr was 66% higher and Cmax was 5% higher following a moderate-fat meal compared to fasting. Administration of raltegravir following a high-fat meal (825 Kcal, 52 g fat) increased AUC and Cmax by approximately 2-fold and increased C12hr by 4.1-fold. Administration of raltegravir following a low-fat meal (300 Kcal, 2.5 g fat) decreased AUC and Cmax by 46% and 52%, respectively; C12hr was essentially unchanged. Food appears to increase pharmacokinetic variability relative to fasting.

Distribution

Raltegravir is approximately 83% bound to human plasma protein over the concentration range of 2 to 10 µM.

Metabolism and Excretion

The apparent terminal half-life of raltegravir is approximately 9 hours, with a shorter α-phase half-life (~1 hour) accounting for much of the AUC. Following administration of an oral dose of radiolabeled raltegravir, approximately 51 and 32% of the dose was excreted in feces and urine, respectively. In feces, only raltegravir was present, most of which is likely derived from hydrolysis of raltegravir-glucuronide secreted in bile as observed in preclinical species. Two components, namely raltegravir and raltegravir-glucuronide, were detected in urine and accounted for approximately 9 and 23% of the dose, respectively. The major circulating entity was raltegravir and represented approximately 70% of the total radioactivity; the remaining radioactivity in plasma was accounted for by raltegravir-glucuronide. Studies using isoform-selective chemical inhibitors and cDNA-expressed UDP-glucuronosyltransferases (UGT) show that UGT1A1 is the main enzyme responsible for the formation of raltegravir-glucuronide. Thus, the data indicate that the major mechanism of clearance of raltegravir in humans is UGT1A1-mediated glucuronidation.

Special Populations

Pediatric

The pharmacokinetics of raltegravir in pediatric patients has not been established.

Age

The effect of age on the pharmacokinetics of raltegravir was evaluated in the composite analysis. No dosage adjustment is necessary.

Race

The effect of race on the pharmacokinetics of raltegravir was evaluated in the composite analysis. No dosage adjustment is necessary.

Gender

A study of the pharmacokinetics of raltegravir was performed in young healthy males and females. Additionally, the effect of gender was evaluated in a composite analysis of pharmacokinetic data from 103 healthy subjects and 28 HIV-1 infected subjects receiving raltegravir monotherapy with fasted administration. No dosage adjustment is necessary.

Hepatic Impairment

Raltegravir is eliminated primarily by glucuronidation in the liver. A study of the pharmacokinetics of raltegravir was performed in subjects with moderate hepatic impairment. Additionally, hepatic impairment was evaluated in the composite pharmacokinetic analysis. There were no clinically important pharmacokinetic differences between subjects with moderate hepatic impairment and healthy subjects. No dosage adjustment is necessary for patients with mild to moderate hepatic impairment. The effect of severe hepatic impairment on the pharmacokinetics of raltegravir has not been studied.

Renal Impairment

Renal clearance of unchanged drug is a minor pathway of elimination. A study of the pharmacokinetics of raltegravir was performed in subjects with severe renal impairment. Additionally, renal impairment was evaluated in the composite pharmacokinetic analysis. There were no clinically important pharmacokinetic differences between subjects with severe renal impairment and healthy subjects. No dosage adjustment is necessary. Because the extent to which ISENTRESS may be dialyzable is unknown, dosing before a dialysis session should be avoided.

UGT1A1 Polymorphism

There is no evidence that common UGT1A1 polymorphisms alter raltegravir pharmacokinetics to a clinically meaningful extent. In a comparison of 30 subjects with *28/*28 genotype (associated with reduced activity of UGT1A1) to 27 subjects with wild-type genotype, the geometric mean ratio (90% CI) of AUC was 1.41 (0.96, 2.09).

Drug Interactions [see Drug Interactions (7)]

Table 7: Effect of Other Agents on the Pharmacokinetics of Raltegravir
Coadministered Drug | Coadministered Drug Dose/Schedule | Raltegravir Dose/Schedule | Ratio (90% Confidence Interval) of Raltegravir Pharmacokinetic Parameters with/without Coadministered Drug; No Effect = 1.00
Coadministered Drug | Coadministered Drug Dose/Schedule | Raltegravir Dose/Schedule | n | Cmax | AUC | Cmin
atazanavir | 400 mg daily | 100 mg single dose | 10 | 1.53 (1.11, 2.12) | 1.72 (1.47, 2.02) | 1.95 (1.30, 2.92)
atazanavir/ritonavir | 300 mg/100 mg daily | 400 mg twice daily | 10 | 1.24 (0.87, 1.77) | 1.41 (1.12, 1.78) | 1.77 (1.39, 2.25)
efavirenz | 600 mg daily | 400 mg single dose | 9 | 0.64 (0.41, 0.98) | 0.64 (0.52, 0.80) | 0.79 (0.49, 1.28)
etravirine | 200 mg twice daily | 400 mg twice daily | 19 | 0.89 (0.68, 1.15) | 0.90 (0.68, 1.18) | 0.66 (0.34, 1.26)
omeprazole | 20 mg daily | 400 mg single dose | 14 (10 for AUC) | 4.15 (2.82, 6.10) | 3.12 (2.13, 4.56) | 1.46 (1.10, 1.93)
rifampin | 600 mg daily | 400 mg single dose | 9 | 0.62 (0.37, 1.04) | 0.60 (0.39, 0.91) | 0.39 (0.30, 0.51)
rifampin | 600 mg daily | 400 mg twice daily when administered alone; 800 mg twice daily when administered with rifampin | 14 | 1.62 (1.12, 2.33) | 1.27 (0.94, 1.71) | 0.47 (0.36, 0.61)
ritonavir | 100 mg twice daily | 400 mg single dose | 10 | 0.76 (0.55, 1.04) | 0.84 (0.70, 1.01) | 0.99 (0.70 1.40)
tenofovir | 300 mg daily | 400 mg twice daily | 9 | 1.64 (1.16, 2.32) | 1.49 (1.15, 1.94) | 1.03 (0.73, 1.45)
tipranavir/ritonavir | 500 mg/200 mg twice daily | 400 mg twice daily | 15 (14 for Cmin) | 0.82 (0.46, 1.46) | 0.76 (0.49, 1.19) | 0.45 (0.31, 0.66)

12.4 Microbiology

Mechanism of Action

Raltegravir inhibits the catalytic activity of HIV-1 integrase, an HIV-1 encoded enzyme that is required for viral replication. Inhibition of integrase prevents the covalent insertion, or integration, of unintegrated linear HIV-1 DNA into the host cell genome preventing the formation of the HIV-1 provirus. The provirus is required to direct the production of progeny virus, so inhibiting integration prevents propagation of the viral infection. Raltegravir did not significantly inhibit human phosphoryltransferases including DNA polymerases α, β, and γ.

Antiviral Activity in Cell Culture

Raltegravir at concentrations of 31 ± 20 nM resulted in 95% inhibition (EC95) of viral spread (relative to an untreated virus-infected culture) in human T-lymphoid cell cultures infected with the cell-line adapted HIV-1 variant H9IIIB. In addition, 5 clinical isolates of HIV-1 subtype B had EC95 values ranging from 9 to 19 nM in cultures of mitogen-activated human peripheral blood mononuclear cells. In a single-cycle infection assay, raltegravir inhibited infection of 23 HIV-1 isolates representing 5 non-B subtypes (A, C, D, F, and G) and 5 circulating recombinant forms (AE, AG, BF, BG, and cpx) with EC50 values ranging from 5 to 12 nM. Raltegravir also inhibited replication of an HIV-2 isolate when tested in CEMx174 cells (EC95 value = 6 nM). Additive to synergistic antiretroviral activity was observed when human T-lymphoid cells infected with the H9IIIB variant of HIV-1 were incubated with raltegravir in combination with non-nucleoside reverse transcriptase inhibitors (delavirdine, efavirenz, or nevirapine); nucleoside analog reverse transcriptase inhibitors (abacavir, didanosine, lamivudine, stavudine, tenofovir, zalcitabine, or zidovudine); protease inhibitors (amprenavir, atazanavir, indinavir, lopinavir, nelfinavir, ritonavir, or saquinavir); or the entry inhibitor enfuvirtide.

Resistance

The mutations observed in the HIV-1 integrase coding sequence that contributed to raltegravir resistance (evolved either in cell culture or in subjects treated with raltegravir) generally included an amino acid substitution at either Q148 (changed to H, K, or R) or N155 (changed to H) plus one or more additional substitutions (i.e., L74M, E92Q, T97A, E138A/K, G140A/S, V151I, G163R, H183P, Y226C/D/F/H, S230R and D232N). Amino acid substitution at Y143C/H/R is another pathway to raltegravir resistance.

Treatment-Naïve Subjects: By Week 48 in the STARTMRK trial, the primary raltegravir resistance-associated substitutions were observed in 3 (1 with Y143R and 2 with Q148H/R) of the 6 virologic failure subjects with evaluable paired genotypic data.

Treatment-Experienced Subjects: By Week 48 in the BENCHMRK trials, at least one of the 3 primary raltegravir resistance-associated substitutions, Y143C/H/R, Q148H/K/R, and N155H, was observed in 63 (64.3%) of the 98 virologic failure subjects with evaluable genotypic data from paired baseline and raltegravir treatment-failure isolates. Some (n=18) of those HIV-1 isolates harboring one or more of the 3 primary raltegravir resistance-associated substitutions were evaluated for raltegravir susceptibility yielding a median decrease of 47.3-fold (mean 73.1 ± 60.8-fold decrease, ranging from 0.9- to 200-fold) compared to baseline isolates.

13 NONCLINICAL TOXICOLOGY

13.1 Carcinogenesis, Mutagenesis, Impairment of Fertility

Carcinogenicity studies of raltegravir in mice did not show any carcinogenic potential. At the highest dose levels, 400 mg/kg/day in females and 250 mg/kg/day in males, systemic exposure was 1.8-fold (females) or 1.2-fold (males) greater than the AUC (54 µM●hr) at the 400-mg twice daily human dose. Treatment-related squamous cell carcinoma of nose/nasopharynx was observed in female rats dosed with 600 mg/kg/day raltegravir for 104 weeks. These tumors were possibly the result of local irritation and inflammation due to local deposition and/or aspiration of drug in the mucosa of the nose/nasopharynx during dosing. No tumors of the nose/nasopharynx were observed in rats dosed with 150 mg/kg/day (males) and 50 mg/kg/day (females) and the systemic exposure in rats was 1.7-fold (males) to 1.4-fold (females) greater than the AUC (54 μM●hr) at the 400-mg twice daily human dose.

No evidence of mutagenicity or genotoxicity was observed in in vitro microbial mutagenesis (Ames) tests, in vitro alkaline elution assays for DNA breakage and in vitro and in vivo chromosomal aberration studies.

No effect on fertility was seen in male and female rats at doses up to 600 mg/kg/day which resulted in 3.0-fold exposure above the exposure at the recommended human dose.

14 CLINICAL STUDIES

Description of Clinical Studies

The evidence of durable efficacy of ISENTRESS is based on the analyses of 48-week data from an ongoing, randomized, double-blind, active-control trial, STARTMRK (Protocol 021) in antiretroviral treatment-naive HIV-1 infected adult subjects and from 2 ongoing, randomized, double-blind, placebo-controlled studies, BENCHMRK 1 and BENCHMRK 2 (Protocols 018 and 019), in antiretroviral treatment-experienced HIV-1 infected adult subjects. These efficacy results were supported by the 96-week analysis of a randomized, double-blind, controlled, dose-ranging trial, Protocol 004, in antiretroviral treatment-naïve HIV-1 infected adult subjects and by the 48-week analysis of a randomized, double-blind, controlled, dose-ranging study, Protocol 005, in antiretroviral treatment-experienced HIV-1 infected adult subjects.

Treatment-Naïve Subjects

STARTMRK (Protocol 021) is a Phase 3 study to evaluate the safety and antiretroviral activity of ISENTRESS 400 mg twice daily + emtricitabine (+) tenofovir versus efavirenz 600 mg at bedtime plus emtricitabine (+) tenofovir in treatment-naïve HIV-1-infected subjects with HIV-1 RNA >5000 copies/mL. Randomization was stratified by screening HIV-1 RNA level (≤50,000 copies/mL; and >50,000 copies/mL) and by hepatitis status.

Table 8 shows the demographic characteristics of subjects in the group receiving ISENTRESS 400 mg twice daily and subjects in the comparator group.

Table 8: Baseline Characteristics
Randomized Study | ISENTRESS | Efavirenz
Protocol 021 | 400 mg Twice Daily | 600 mg At Bedtime
 | (N = 281) | (N = 282)
Gender
Male | 81% | 82%
Female | 19% | 18%
Race
White | 41% | 44%
Black | 12% | 8%
Asian | 13% | 11%
Hispanic | 21% | 24%
Native American | 0% | 0%
Multiracial | 12% | 13%
Region
Latin America | 35% | 34%
Southeast Asia | 12% | 10%
North America | 29% | 32%
EU/Australia | 23% | 23%
Age (years)
18-64 | 99% | 99%
≥65 | 1% | 1%
Mean (SD) | 38 (9) | 37 (10)
Median (min, max) | 37 (19 to 67) | 36 (19 to 71)
CD4 Cell Count (cells/microL)
Mean (SD) | 219 (124) | 217 (134)
Median (min, max) | 212 (1 to 620) | 204 (4 to 807)
Plasma HIV-1 RNA (log10 copies/mL)
Mean (SD) | 5 (1) | 5 (1)
Median (min, max) | 5 (3 to 6) | 5 (4 to 6)
Plasma HIV-1 RNA (copies/mL)
Geometric Mean | 103205 | 106215
Median (min, max) | 114000 (400 to 750000) | 104000 (4410 to 750000)
History of AIDS [Includes additional subjects identified as having a history of AIDS.]
Yes | 18% | 21%
Viral Subtype
Clade B | 78% | 82%
Non-Clade B [Non-Clade B Subtypes (# of subjects): Clade A (4), A/C (1), A/G (2), A1 (1), AE (29), AG (12), BF (6), C (37), D (2), F (2), F1 (5), G (2), Complex (3).] | 21% | 17%
Baseline Plasma HIV-1 RNA
≤100,000 copies/mL | 45% | 49%
>100,000 copies/mL | 55% | 51%
Baseline CD4 Cell Counts
≤50 cells/mm^3 | 10% | 11%
>50 cells/mm^3 and ≤ 200 cells/mm^3 | 37% | 37%
>200 cells/mm^3 | 53% | 51%
Hepatitis Status
Hepatitis B or C Positive [Evidence of hepatitis B surface antigen or evidence of HCV RNA by polymerase chain reaction (PCR) quantitative test for hepatitis C Virus.] | 6% | 6%
Notes:
ISENTRESS and Efavirenz were administered with emtricitabine (+) tenofovir
N = Number of subjects in each group.

Week 48 outcomes from Protocol 021 are shown in Table 9.

Table 9: Outcomes by Treatment Group through Week 48
Randomized Study; Protocol 021 | ISENTRESS 400 mg; Twice Daily; (N = 281) | Efavirenz; 600 mg; At Bedtime; (N = 282) | Difference; (ISENTRESS – Efavirenz) (CI [The 95% CI for treatment difference is adjusted by the screening HIV RNA level (<=50,000 copies/mL vs. >50,000 copies/mL) and Hepatitis B or C (negative vs. positive)])
Outcome at Week 48
Subjects with HIV-1 RNA less than 50 copies/mL | 87% | 82% | 4.7% (-1.3%, 10.6%)
Subjects with HIV-1 RNA less than 400 copies/mL | 91% | 88% | 3.6% (-1.5%, 8.7%)
Mean CD4 cell count change from baseline (cells/mm^3) | 176 | 150 | 25.8 (5.0, 46.5)
Virologic Failure (>50 copies/mL) | 6% | 7%
Never suppressed through Week 48 and on study at Week 48 | 2% | 3%
Rebound | 5% | 5%
Discontinued study drug | 7% | 10%
Reasons for Discontinuation
Death | <1% | 0%
Adverse experiences | 2% | 5%
Other [Other includes lack of efficacy, loss to follow-up, consent withdrawn, protocol violation and other] | 4% | 5%

Treatment-Experienced Subjects

BENCHMRK 1 and BENCHMRK 2 are Phase 3 studies to evaluate the safety and antiretroviral activity of ISENTRESS 400 mg twice daily in combination with an optimized background therapy (OBT), versus OBT alone, in HIV-1-infected subjects, 16 years or older, with documented resistance to at least 1 drug in each of 3 classes (NNRTIs, NRTIs, PIs) of antiretroviral therapies. Randomization was stratified by degree of resistance to PI (1PI vs. >1PI) and the use of enfuvirtide in the OBT. Prior to randomization, OBT was selected by the investigator based on genotypic/phenotypic resistance testing and prior ART history.

Table 10 shows the demographic characteristics of subjects in the group receiving ISENTRESS 400 mg twice daily and subjects in the placebo group.

Table 10: Baseline Characteristics
Randomized Studies Protocol 018 and 019 | ISENTRESS 400 mg Twice Daily + OBT (N = 462) | Placebo + OBT (N = 237)
Gender
Male | 88% | 89%
Female | 12% | 11%
Race
White | 65% | 73%
Black | 14% | 11%
Asian | 3% | 3%
Hispanic | 11% | 8%
Others | 6% | 5%
Age (years)
Median (min, max) | 45 (16 to 74) | 45 (17 to 70)
CD4+ Cell Count
Median (min, max), cells/mm^3 | 119 (1 to 792) | 123 (0 to 759)
≤50 cells/mm^3 | 32% | 33%
>50 and ≤200 cells/mm^3 | 37% | 36%
Plasma HIV-1 RNA
Median (min, max), log10 copies/mL | 4.8 (2 to 6) | 4.7 (2 to 6)
>100,000 copies/mL | 35% | 33%
History of AIDS
Yes | 92% | 91%
Prior Use of ART, Median (1st Quartile, 3rd Quartile)
Years of ART Use | 10 (7 to 12) | 10 (8 to 12)
Number of ART | 12 (9 to 15) | 12 (9 to 14)
Hepatitis Co-infection [Hepatitis B virus surface antigen positive or hepatitis C virus antibody positive.]
No Hepatitis B or C virus | 83% | 85%
Hepatitis B virus only | 8% | 3%
Hepatitis C virus only | 8% | 11%
Co-infection of Hepatitis B and C virus | 1% | 1%
Stratum
Enfuvirtide in OBT | 38% | 38%
Resistant to ≥2 PI | 97% | 95%

Table 11 compares the characteristics of optimized background therapy at baseline in the group receiving ISENTRESS 400 mg twice daily and subjects in the control group.

Table 11: Characteristics of Optimized Background Therapy at Baseline
Randomized Studies Protocol 018 and 019 | ISENTRESS 400 mg Twice Daily + OBT (N = 462) | Placebo + OBT (N = 237)
Number of ARTs in OBT
Median (min, max) | 4 (1 to 7) | 4 (2 to 7)
Number of Active PI in OBT by
Phenotypic Resistance Test [Darunavir use in OBT in darunavir naïve subjects was counted as one active PI.]
0 | 36% | 41%
1 or more | 60% | 58%
Phenotypic Sensitivity Score (PSS) [The Phenotypic Sensitivity Score (PSS) and the Genotypic Sensitivity Score (GSS) were defined as the total oral ARTs in OBT to which a subject's viral isolate showed phenotypic sensitivity and genotypic sensitivity, respectively, based upon phenotypic and genotypic resistance tests. Enfuvirtide use in OBT in enfuvirtide-naïve subjects was counted as one active drug in OBT in the GSS and PSS. Similarly, darunavir use in OBT in darunavir-naïve subjects was counted as one active drug in OBT.]
0 | 15% | 19%
1 | 31% | 30%
2 | 31% | 28%
3 or more | 18% | 20%
Genotypic Sensitivity Score (GSS)
0 | 25% | 28%
1 | 39% | 41%
2 | 24% | 21%
3 or more | 11% | 10%

Week 48 outcomes for the 699 subjects randomized and treated with the recommended dose of ISENTRESS 400 mg twice daily or placebo in the pooled BENCHMRK 1 and 2 studies are shown in Table 12.

Table 12: Outcomes by Treatment Group through Week 48
Randomized Studies Protocol 018 and 019 | ISENTRESS 400 mg Twice Daily + OBT (N = 462) | Placebo + OBT (N = 237)
Outcome at Week 48
Subjects with HIV-1 RNA less than 400 copies/mL | 72% | 37%
Subjects with HIV-1 RNA less than 50 copies/mL | 60% | 31%
Mean CD4 cell count change from baseline (cells/mm^3) | 106 | 44
Virologic Failure (>50 copies/mL) | 36% | 65%
Never suppressed through Week 48 and on study at Week 48 | 11% | 9%
Rebound | 13% | 8%
Non-responder by Week 48 [The non-responders by Week 48 were defined by the protocol as those who did not achieve > 1.0 log10 HIV-1 RNA reduction and <400 HIV-1 RNA copies/mL starting at Week 16 or beyond.] | 12% | 48%
Discontined study drug | 4% | 4%
Reasons for Discontinuation
Death | 2% | 2%
Adverse Experiences | <1% | <1%
Other [Other includes lack of efficacy, loss to follow-up, consent withdrawn] | 2% | 1%

The mean changes in plasma HIV-1 RNA from baseline were -2.11 log10 copies/mL in the group receiving ISENTRESS 400 mg twice daily and -0.96 log10 copies/mL for the control group.

Treatment-emergent CDC Category C events occurred in 4% of the group receiving ISENTRESS 400 mg twice daily and 5% of the control group.

Virologic responses at Week 48 by baseline genotypic and phenotypic sensitivity score are shown in Table 13.

Table 13: Virologic Response at Week 48 by Baseline Genotypic/Phenotypic Sensitivity Score
Randomized Studies Protocol 018 and 019 | Percent with HIV-1 RNA <400 copies/mL at Week 48 |  |  |  | Percent with HIV-1 RNA <50 copies/mL at Week 48
Randomized Studies Protocol 018 and 019 | n | ISENTRESS 400 mg Twice Daily + OBT (N = 462) | n | Placebo; + OBT; (N = 237) | n | ISENTRESS 400 mg Twice Daily + OBT (N = 462) | n | Placebo; + OBT; (N = 237)
Phenotypic Sensitivity Score (PSS) [The Phenotypic Sensitivity Score (PSS) and the Genotypic Sensitivity Score (GSS) were defined as the total oral ARTs in OBT to which a subject's viral isolate showed phenotypic sensitivity and genotypic sensitivity, respectively, based upon phenotypic and genotypic resistance tests. Enfuvirtide use in OBT in enfuvirtide-naïve subjects was counted as one active drug in OBT in the GSS and PSS. Similarly, darunavir use in OBT in darunavir-naïve subjects was counted as one active drug in OBT.]
0 | 69 | 52 | 44 | 5 | 69 | 46 | 44 | 2
1 | 145 | 72 | 72 | 32 | 145 | 57 | 72 | 28
2 | 142 | 83 | 66 | 42 | 142 | 68 | 66 | 38
3 or more | 85 | 72 | 48 | 60 | 85 | 67 | 48 | 46
Genotypic Sensitivity Score (GSS)
0 | 115 | 50 | 66 | 8 | 115 | 43 | 66 | 3
1 | 178 | 79 | 96 | 38 | 178 | 63 | 96 | 35
2 | 111 | 85 | 49 | 65 | 111 | 70 | 49 | 53
3 or more | 51 | 69 | 23 | 52 | 51 | 67 | 23 | 39

16 HOW SUPPLIED/STORAGE AND HANDLING

ISENTRESS tablets 400 mg are pink, oval-shaped, film-coated tablets with “227” on one side.

They are supplied by State of Florida DOH Central Pharmacy as follows:

NDC | Strength | Quantity/Form | Color | Source Prod. Code
53808-0650-1 | 400 mg | 30 Tablets in a Blister Pack | pink | 0006-0227

Storage and Handling

Store at 20-25°C (68-77°F); excursions permitted to 15-30°C (59-86°F). See USP Controlled Room Temperature.

17 PATIENT COUNSELING INFORMATION

[See FDA-Approved Patient Labeling.]

Patients should be informed that ISENTRESS is not a cure for HIV infection or AIDS. They should also be told that people taking ISENTRESS may still get infections or other conditions common in people with HIV (opportunistic infections). Patients should also be told that it is very important that they stay under a physician's care during treatment with ISENTRESS.

Patients should be informed that ISENTRESS does not reduce the chance of passing HIV to others through sexual contact, sharing needles, or being exposed to blood. Patients should be advised to continue to practice safer sex and to use latex or polyurethane condoms or other barrier methods to lower the chance of sexual contact with any body fluids such as semen, vaginal secretions or blood. Patients should also be advised to never re-use or share needles.

Physicians should instruct their patients that if they miss a dose, they should take it as soon as they remember. If they do not remember until it is time for the next dose, they should be instructed to skip the missed dose and go back to the regular schedule. Patients should not take two tablets of ISENTRESS at the same time.

Physicians should instruct their patients to read the Patient Package Insert before starting ISENTRESS therapy and to reread each time the prescription is renewed. Patients should be instructed to inform their physician or pharmacist if they develop any unusual symptom, or if any known symptom persists or worsens.

Manufactured and Distributed by:
MERCK & CO., INC., Whitehouse Station, NJ 08889, USA

U.S. Patent Nos. US 7,169,780

This Product was Repackaged By:

State of Florida DOH Central Pharmacy
104-2 Hamilton Park Drive
Tallahassee, FL 32304
United States

FDA-Approved Patient Labeling

Patient Information
ISENTRESS® (eye sen tris)
(raltegravir)
Tablets

Read the patient information that comes with ISENTRESS before you start taking it and each time you get a refill. There may be new information. This leaflet is a summary of the information for patients. Your doctor or pharmacist can give you additional information. This leaflet does not take the place of talking with your doctor about your medical condition or your treatment.

What is ISENTRESS?

- ISENTRESS is an anti-HIV (antiretroviral) medicine used for the treatment of HIV. The term HIV stands for Human Immunodeficiency Virus. It is the virus that causes AIDS (Acquired Immune Deficiency Syndrome). ISENTRESS is used along with other anti-HIV medicines. ISENTRESS will NOT cure HIV infection.
- People taking ISENTRESS may still develop infections, including opportunistic infections or other conditions that happen with HIV infection.
- Stay under the care of your doctor during treatment with ISENTRESS.
- The safety and effectiveness of ISENTRESS in children has not been studied.

ISENTRESS must be used with other anti-HIV medicines.

How does ISENTRESS work?

- ISENTRESS blocks an enzyme which the virus (HIV) needs in order to make more virus. The enzyme that ISENTRESS blocks is called HIV integrase.
- When used with other anti-HIV medicines, ISENTRESS may do two things:
  1. Reduce the amount of HIV in your blood. This is called your "viral load".
  2. Increase the number of white blood cells called CD4 (T) cells.
- ISENTRESS may not have these effects in all patients.

Does ISENTRESS lower the chance of passing HIV to other people?

No. ISENTRESS does not reduce the chance of passing HIV to others through sexual contact, sharing needles, or being exposed to your blood.

- Continue to practice safer sex.
- Use latex or polyurethane condoms or other barrier methods to lower the chance of sexual contact with any body fluids. This includes semen from a man, vaginal secretions from a woman, or blood.
- Never re-use or share needles.

Ask your doctor if you have any questions about safer sex or how to prevent passing HIV to other people.

What should I tell my doctor before and during treatment with ISENTRESS?

Tell your doctor about all of your medical conditions. Include any of the following that applies to you:

- You have any allergies.
- You are pregnant or plan to become pregnant.
  - ISENTRESS is not recommended for use during pregnancy. ISENTRESS has not been studied in pregnant women. If you take ISENTRESS while you are pregnant, talk to your doctor about how you can be included in the Antiretroviral Pregnancy Registry.
- You are breast-feeding or plan to breast-feed.
  - It is recommended that HIV-infected women should not breast-feed their infants. This is because their babies could be infected with HIV through their breast milk.
  - Talk with your doctor about the best way to feed your baby.

Tell your doctor about all the medicines you take. Include the following:

- prescription medicines, including rifampin (a medicine used to treat some infections such as tuberculosis)
- non-prescription medicines
- vitamins
- herbal supplements

Know the medicines you take.

- Keep a list of your medicines. Show the list to your doctor and pharmacist when you get a new medicine.

How should I take ISENTRESS?

Take ISENTRESS exactly as your doctor has prescribed. The recommended dose is as follows:

- Take only one 400-mg tablet at a time.
- Take it twice a day.
- Take it by mouth.
- Take it with or without food.

Do not change your dose or stop taking ISENTRESS or your other anti-HIV medicines without first talking with your doctor.

IMPORTANT: Take ISENTRESS exactly as your doctor prescribed and at the right times of day because if you don't:

- The amount of virus (HIV) in your blood may increase if the medicine is stopped for even a short period of time.
- The virus may develop resistance to ISENTRESS and become harder to treat.
- Your medicines may stop working to fight HIV.
- The activity of ISENTRESS may be reduced (due to resistance).

If you fail to take ISENTRESS the way you should, here's what to do:

- If you miss a dose, take it as soon as you remember. If you do not remember until it is time for your next dose, skip the missed dose and go back to your regular schedule. Do NOT take two tablets of ISENTRESS at the same time. In other words, do NOT take a double dose.
- If you take too much ISENTRESS, call your doctor or local Poison Control Center.

Be sure to keep a supply of your anti-HIV medicines.

- When your ISENTRESS supply starts to run low, get more from your doctor or pharmacy.
- Do not wait until your medicine runs out to get more.

What are the possible side effects of ISENTRESS?

When ISENTRESS has been given with other anti-HIV drugs, the most common side effects included:

- nausea
- headache
- tiredness
- weakness
- trouble sleeping

Other side effects include rash, severe skin reactions, feeling anxious, depression, suicidal thoughts and actions, paranoia.

A condition called Immune Reconstitution Syndrome can happen in some patients with advanced HIV infection (AIDS) when combination antiretroviral treatment is started. Signs and symptoms of inflammation from opportunistic infections that a person has or had may occur as the medicines work to treat the HIV infection and help to strengthen the immune system. Call your doctor right away if you notice any signs or symptoms of an infection after starting ISENTRESS with other anti-HIV medicines.

Contact your doctor promptly if you experience unexplained muscle pain, tenderness, or weakness while taking ISENTRESS. This is because on rare occasions, muscle problems can be serious and can lead to kidney damage.

Tell your doctor if you have any side effects that bother you.

These are not all the side effects of ISENTRESS. For more information, ask your doctor or pharmacist.

How should I store ISENTRESS?

- Store ISENTRESS at room temperature (68 to 77°F).
- Keep ISENTRESS and all medicines out of the reach of children.

General information about the use of ISENTRESS

Medicines are sometimes prescribed for conditions that are not mentioned in patient information leaflets.

- Do not use ISENTRESS for a condition for which it was not prescribed.
- Do not give ISENTRESS to other people, even if they have the same symptoms you have. It may harm them.

This leaflet gives you the most important information about ISENTRESS.

- If you would like to know more, talk with your doctor.
- You can ask your doctor or pharmacist for additional information about ISENTRESS that is written for health professionals.
- For more information go to www.ISENTRESS.com or call 1-800-622-4477.

What are the ingredients in ISENTRESS?

Active ingredient: Each film-coated tablet contains 400 mg of raltegravir.

Inactive ingredients: Microcrystalline cellulose, lactose monohydrate, calcium phosphate dibasic anhydrous, hypromellose 2208, poloxamer 407 (contains 0.01% butylated hydroxytoluene as antioxidant), sodium stearyl fumarate, magnesium stearate. In addition, the film coating contains the following inactive ingredients: polyvinyl alcohol, titanium dioxide, polyethylene glycol 3350, talc, red iron oxide and black iron oxide.

Manufactured and Distributed by:
MERCK & CO., Inc.
Whitehouse Station, NJ 08889, USA

U.S. Patent Nos. US 7,169,780

This Product was Repackaged By:

State of Florida DOH Central Pharmacy
104-2 Hamilton Park Drive
Tallahassee, FL 32304
United States

PACKAGE LABEL

PRINCIPAL DISPLAY PANEL - 400 mg

Isentress™
(raltegravir) tablets

400 mg

Each tablet contains 434.4 mg raltegravir potassium, equivalent to 400 mg raltegravir.

Rx only

60 Tablets

NDC 53808-0650-1

Store at 20-25°C (68-77°F); excursions permitted to 15-30°C (59-86°F). See USP Controlled Room Temperature.

USUAL ADULT DOSAGE:
See accompanying circular.

MERCK & CO., INC.
Whitehouse Station, NJ 08889, USA

Raltegravir potassium (active ingred.)
Made in Ireland

Formulated in USA